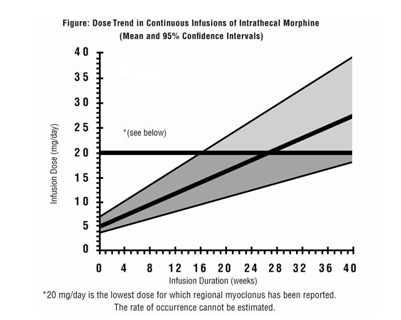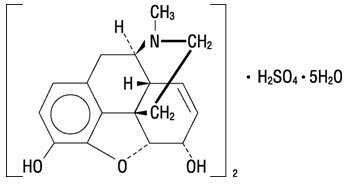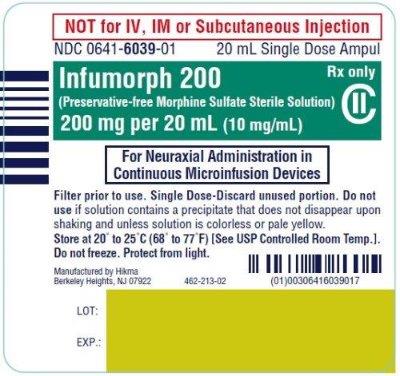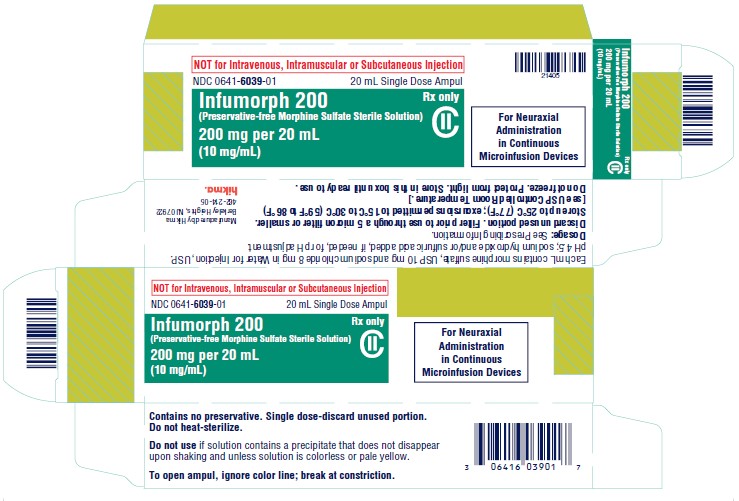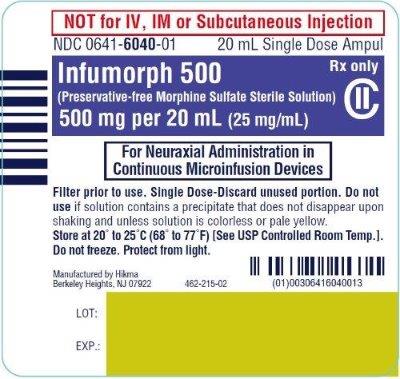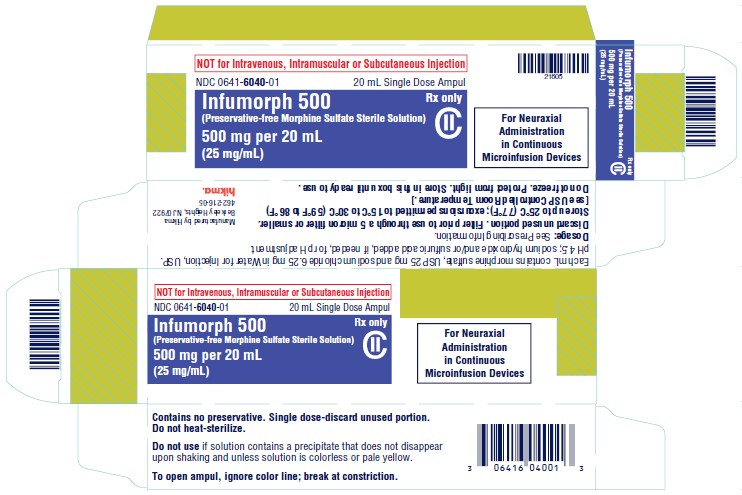 DRUG LABEL: INFUMORPH 200
NDC: 0641-6039 | Form: INJECTION, SOLUTION
Manufacturer: Hikma Pharmaceuticals USA Inc.
Category: prescription | Type: HUMAN PRESCRIPTION DRUG LABEL
Date: 20251231
DEA Schedule: CII

ACTIVE INGREDIENTS: MORPHINE SULFATE 10 mg/1 mL
INACTIVE INGREDIENTS: SODIUM CHLORIDE 8 mg/1 mL; WATER; SODIUM HYDROXIDE; SULFURIC ACID

HIGHLIGHTS OF PRESCRIBING INFORMATION

These highlights do not include all the information needed to use INFUMORPH safely and effectively. See full prescribing information for INFUMORPH.
INFUMORPH (morphine sulfate), Preservative-free, injectable solution, for intrathecal or epidural infusion, using a continuous microinfusion device, CII
Initial U.S. Approval: 1941

WARNING: SERIOUS AND LIFE-THREATENING RISKS FROM USE OF INFUMORPH

See full prescribing information for complete boxed warning.

- Single-dose neuraxial administration may result in acute or delayed respiratory depression up to 24 hours. Because of the risk of severe adverse reactions when INFUMORPH is administered by the epidural or intrathecal route of administration, patients must be observed in a fully equipped and staffed environment for at least 24 hours after the initial dose. (5.1)
- INFUMORPH exposes users to the risks of opioid addiction, abuse, and misuse, which can lead to overdose and death. Assess patient’s risk before prescribing and reassess regularly for these behaviors and conditions. (5.2)
- Serious, life-threatening, or fatal respiratory depression may occur with use of INFUMORPH, especially during initiation or following a dosage increase. To reduce the risk of respiratory depression, proper dosing and titration of INFUMORPH are essential. (5.3)
- Concomitant use of opioids with benzodiazepines or other central nervous system (CNS) depressants, including alcohol, may result in profound sedation, respiratory depression, coma, and death. Reserve concomitant prescribing for use in patients for whom alternative treatment options are inadequate. (5.4, 7)
- Advise pregnant women using opioids for an extended period of time of the risk of Neonatal Opioid Withdrawal Syndrome, which may be life-threatening if not recognized and treated. Ensure that management by neonatology experts will be available at delivery. (5.5)

RECENT MAJOR CHANGES

Boxed Warnings 12/2025
Indications and Usage (1) 12/2025
Dosage and Administration (2.6) 12/2025
Warnings and Precautions (5.2, 5.3, 5.4, 5.14, 5.16) 12/2025

1 INDICATIONS AND USAGE

INFUMORPH is an opioid agonist, for use in continuous microinfusion devices and indicated only for intrathecal or epidural infusion in the management of intractable chronic pain severe enough to require an opioid analgesic and for which alternative treatments are inadequate. (1)

Limitations of Use:
Not for single-dose intravenous, intramuscular, or subcutaneous administration due to the risk of overdose.

Not for single-dose neuraxial injection because INFUMORPH is too concentrated for accurate delivery of the smaller doses used in this setting. (1)

2 DOSAGE AND ADMINISTRATION

- INFUMORPH should be prescribed only by healthcare professionals who are knowledgeable about the use of opioids and how to mitigate the associated risks. (2.1)
- Should be administered by or under the direction of a physician experienced in the techniques of epidural or intrathecal administration. (2.1)
- Patients should be observed in a fully equipped and staffed environmentforatleast24hoursaftereachtestdoseand,as indicated, for the first several days after surgery. (2.1)
- Use the lowest effective dosage for the shortest duration of time consistent with individual patient treatment goals. Reserve titration to higher doses of INFUMORPH for patients in whom lower doses are insufficiently effective and in whom the expected benefits of using a higher dose opioid clearly outweigh the substantial risks. (2.1, 5)
- Initiate the dosing regimen for each patient individually, taking into account the patient’s underlying cause and severity of pain, prior analgesic treatment and response, and risk factors for addiction, abuse, and misuse. (2.1, 5.2)
- Respiratory depression can occur at any time during opioid therapy, especially when initiating and following dosage increases with INFUMORPH. Consider this risk when selecting an initial dose and when making dose adjustments. (2.1, 5.3)
- Initial Dosage: Must be individualized, based upon in-hospital evaluation of the response to serial single dose epidural bolus injections of regular DURAMORPH (morphine sulfate injection, USP) 0.5 mg/mL or 1 mg/mL, with close observation for analgesic efficacy and adverse effects prior to surgery involving the continuous microinfusion device. (2.2)
- Dosage for Epidural Administration: Initial dose range of 3.5 to 7.5 mg/day for patients with no tolerance to opioids. The usual starting dose for continuous epidural infusion in patients with some degree of opioid tolerance is 4.5 to 10 mg/day and may increase significantly during treatment to 20-30 mg/day. (2.3)
- Dosage for Intrathecal Administration: Initial dose range of 0.2 to 1 mg/day for patients with no tolerance to opioids. The range of doses for patients with some degree of opioid tolerance varies from 1 to 10 mg/day. Doses above 20 mg/day should be employed with caution. (2.4)
- Periodically reassess patients receiving INFUMORPH to evaluate the continued need for opioid analgesics to maintain pain control, for signs or symptoms of adverse reactions, and for the development of addiction, abuse or misuse. (2.5)
- Do not rapidly reduce or abruptly discontinue INFUMORPH in a physically-dependent patient. (2.6, 5.16)

3 DOSAGE FORMS AND STRENGTHS

Injection: 200 mg/20 mL (10 mg/mL) Preservative-free amber glass ampuls
Injection: 500 mg/20 mL (25 mg/mL) Preservative-free amber glass ampuls (3)

4 CONTRAINDICATIONS

- Significant respiratory depression (4)
- Acute or severe bronchial asthma in an unmonitored setting in absence of resuscitative equipment (4)
- Concurrent use of monoamine oxidase inhibitors (MAOIs) or use of MAOIs within the last 14 days (4)
- Known or suspected gastrointestinal obstruction, including paralytic ileus (4)
- Hypersensitivity or intolerance to morphine (4)

Neuraxial administration of INFUMORPH is contraindicated in patients with:

- Infection at the injection microinfusion site (4)
- Concomitant anticoagulant therapy (4)
- Uncontrolled bleeding diathesis (4)
- The presence of any other concomitant therapy or medical condition which would render epidural or
- intrathecal administration of medication especially hazardous. (4)

5 WARNINGS AND PRECAUTIONS

- Risk of Inflammatory Masses: Monitor patients receiving continuous infusion of INFUMORPH via indwelling intrathecal catheter for new signs or symptoms of neurologic impairment. (5.6)
- Risk of Tolerance and Myoclonic Activity: Monitor patients for unusual acceleration of neuraxial morphine, which may cause myoclonic-like spasm of lower extremities. Detoxification may be required. (5.7)
- Opioid-Induced Hyperalgesia and Allodynia: Opioid-Induced Hyperalgesia (OIH) occurs when an opioid analgesic paradoxically causes an increase in pain, or an increase in sensitivity to pain. If OIH is suspected, carefully consider appropriately decreasing the dose of the current opioid analgesic or opioid rotation. (5.8)
- Life-Threatening Respiratory Depression in Patients with Chronic Pulmonary Disease or in Elderly, Cachectic, or Debilitated Patients: Monitor closely, particularly during initiation and titration. (5.9)
- Adrenal Insufficiency: If diagnosed, treat with physiologic replacement of corticosteroids, and wean patient off of the opioid. (5.11)
- Severe Hypotension: Monitor during dosage initiation and titration. Avoid use of INFUMORPH in patients with circulatory shock. (5.12)
- Risks of Use in Patients with Increased Intracranial Pressure, Brain Tumors, Head Injury, or Impaired Consciousness: Monitor for sedation and respiratory depression. Avoid use of INFUMORPH in patients with impaired consciousness or coma. (5.13)

6 ADVERSE REACTIONS

Most serious adverse reactions were respiratory depression, apnea, circulatory depression, respiratory arrest, shock, and cardiac arrest.
Other common frequently observed adverse reactions include: sedation, lightheadedness, dizziness, nausea, vomiting, and constipation. (6)

To report SUSPECTED ADVERSE REACTIONS, contact Hikma Pharmaceuticals USA Inc. at 1- 877-845-0689 or FDA at 1-800-FDA-1088 or www.fda.gov/medwatch.

7 DRUG INTERACTIONS

- Serotonergic Drugs: Concomitant use may result in serotonin syndrome. Discontinue INFUMORPH if serotonin syndrome is suspected. (7)
- Mixed Agonist/Antagonist and Partial Agonist Opioid Analgesics: Avoid use with INFUMORPH because they may reduce the effect of INFUMORPH or precipitate withdrawal symptoms. (7)

8 USE IN SPECIFIC POPULATIONS

- Pregnancy: May cause fetal harm. (8.1)
- Hepatic and Renal Impairment: May affect the metabolism and excretion of INFUMORPH. (8.6)

FULL PRESCRIBING INFORMATION

WARNING: SERIOUS AND LIFE-THREATENING RISKS FROM USE OF INFUMORPH

Risks with Neuraxial Administration

Single-dose neuraxial administration may result in acute or delayed respiratory depression up to 24 hours. Because of the risk of severe adverse reactions when INFUMORPH is administered by the epidural or intrathecal route of administration, patients must be observed in a fully equipped and staffed environment for at least 24 hours after the initial dose [see Warnings and Precautions (5.1)].

Addiction, Abuse, and Misuse

Because the use of INFUMORPH exposes patients and other users to the risks of opioid addiction, abuse, and misuse, which can lead to overdose and death, assess each patient’s risk prior to prescribing and reassess all patients regularly for the development of these behaviors and conditions [see Warnings and Precautions (5.2)].

Life-Threatening Respiratory Depression

Serious, life-threatening, or fatal respiratory depression may occur with use of INFUMORPH, especially during initiation or following a dosage increase. To reduce the risk of respiratory depression, proper dosing and titration of INFUMORPH are essential [see Warnings and Precautions (5.3)].

Risks From Concomitant Use With Benzodiazepines Or Other CNS Depressants

Concomitant use of opioids with benzodiazepines or other central nervous system (CNS) depressants, including alcohol, may result in profound sedation, respiratory depression, coma, and death. Reserve concomitant prescribing of INFUMORPH and benzodiazepines or other CNS depressants for use in patients for whom alternative treatment options are inadequate [see Warnings and Precautions (5.4), Drug Interactions (7)].

Neonatal Opioid Withdrawal Syndrome (NOWS)

Advise pregnant women using opioids for an extended period of time of the risk of Neonatal Opioid Withdrawal Syndrome, which may be life threatening if not recognized and treated. Ensure that management by neonatology experts will be available at delivery [see Warnings and Precautions (5.5)].

1 INDICATIONS AND USAGE

INFUMORPH is for use in continuous microinfusion devices and indicated only for intrathecal or epidural infusion in the management of intractable chronic pain severe enough to require an opioid analgesic and for which less invasive means of controlling pain are inadequate.

Limitations of Use
Not for single-dose intravenous, intramuscular, or subcutaneous administration due to the risk of overdose.

Not for single-dose neuraxial injection because INFUMORPH is too concentrated for accurate delivery of the smaller doses used in this setting.

2 DOSAGE AND ADMINISTRATION

2.1 Important Dosage and Administration Instructions

INFUMORPH should be administered by or under the direction of a physician experienced in the techniques of epidural or intrathecal administration and familiar with the patient management problems associated with epidural or intrathecal drug administration.

- INFUMORPH should be prescribed only by healthcare professionals who are knowledgeable about the use of opioids and how to mitigate the associated risks.
- Because of the risk of delayed respiratory depression, patients should be observed in a fully equipped and staffed environment for at least 24 hours after each test dose and, as indicated, for the first several days after surgery.
- Because epidural administration has been associated with less potential for immediate or late adverse effects than intrathecal administration, the epidural route should be used whenever possible.
- For safety reasons, it is recommended that administration of INFUMORPH 200 and 500 (10 and 25 mg/mL, respectively) by the intrathecal route be limited to the lumbar area.
- INFUMORPH 200 and 500 (10 and 25 mg/mL, respectively) should not be used for single-dose neuraxial injection because lower doses can be more reliably administered with the standard preparation of DURAMORPH (0.5 and 1 mg/mL).

Candidates for neuraxial administration of INFUMORPH in a continuous microinfusion device should be hospitalized to provide for adequate patient monitoring during assessment of response to single doses of intrathecal or epidural morphine. Hospitalization should be maintained for several days after surgery involving the infusion device for additional monitoring and adjustment of daily dosage. The facility must be equipped with resuscitative equipment, oxygen, opioid overdose reversal agent (e.g., naloxone, nalmefene) and other resuscitative drugs.

A period of observation appropriate to the clinical situation should follow each refill or manipulation of the drug reservoir. Before discharge, the patient and attendant(s) should receive instruction in the proper home care of the device and insertion site and in the recognition and practical treatment of an overdose of neuraxial morphine.

Familiarization with the continuous microinfusion device is essential. The desired amount of morphine should be withdrawn from the ampul through a microfilter. To minimize risk from glass or other particles, the product must be filtered through a 5 μ (or smaller) microfilter before injecting into the microinfusion device. If dilution is required, 0.9% Sodium Chloride Injection is recommended.

Reservoir filling must be performed by fully trained and qualified personnel, following the directions provided by the device manufacturer. Care should be taken in selecting the proper refill frequency to prevent depletion of the reservoir, which would result in exacerbation of severe pain, onset of opioid withdrawal symptoms, and/or reflux of cerebrospinal fluid into some devices. Strict aseptic technique is required to avoid bacterial contamination and serious infection. Extreme care must be taken to ensure that the needle is properly inserted into the filling port of the device before attempting to refill the reservoir. Injecting the solution into the tissue around the device or (in the case of devices that have more than one port) attempting to inject the refill dose into the direct injection port will result in a large, clinically significant, overdosage to the patient.

Safety and Handling Instructions:

INFUMORPH is supplied in sealed ampuls. Accidental dermal exposure should be treated by the removal of any contaminated clothing and rinsing the affected area with water.

Inspect parenteral drug products for particulate matter before opening the amber ampul and again for color after removing contents from the ampul. Do not use if the solution in the unopened ampul contains a precipitate which does not disappear upon shaking. After removal, do not use unless the solution is colorless or pale yellow.

INFUMORPH is intended for single-use only. Protect from light, discard any unused portion. Do not heat-sterilize.

2.2 Initial Dosage

The starting dose of INFUMORPH must be individualized, based upon in-hospital evaluation of the response to serial single-dose epidural or intrathecal bolus injections of regular DURAMORPH (morphine sulfate injection,) 0.5 mg/mL or 1 mg/mL, with close observation for analgesic efficacy and adverse effects prior to surgery involving the continuous microinfusion device.

- Use the lowest effective dosage for the shortest duration of time consistent with individual patient treatment goals [see Warnings and Precautions (5)]. Because the risk of overdose increases as opioid doses increase, reserve titration to higher doses of INFUMORPH for patients in whom lower doses are insufficiently effective and in whom the expected benefits of using a higher dose opioid clearly outweigh the substantial risks.
- There is variability in the opioid analgesic dose and duration needed to adequately manage pain due both to the cause of pain and to individual patient factors. Initiate the dosing regimen for each patient individually, taking into account the patient’s underlying cause and severity of pain, prior analgesic treatment and response, and risk factors for addiction, abuse, and misuse [see Warnings and Precautions (5.1)].
- Respiratory depression can occur at anytime during opioid therapy, especially when initiating and following dosage increases with INFUMORPH. Consider this risk when selecting an initial dose and when making dose adjustments [see Warnings and Precautions (5)].

2.3 Dosage for Epidural Administration

The recommended initial epidural dose in patients who are not tolerant to opioids ranges from 3.5 to 7.5 mg/day. The usual starting dose for continuous epidural infusion, based upon limited data in patients who have some degree of opioid tolerance, is 4.5 to 10 mg/day. The dose requirements may increase significantly during treatment, frequently to 20-30 mg/day. The upper daily limit for each patient must be individualized.

2.4 Dosage for Intrathecal Administration

The recommended initial lumbar intrathecal dose range in patients with no tolerance to opioids is 0.2 to 1 mg/day. The published range of doses for individuals who have some degree of opioid tolerance varies from 1 to 10 mg/day. The upper daily dosage limit for each patient must be individualized.

- Intrathecal dosage is usually 1/10 that of epidural dosage.

2.5 Titration and Maintenance of Therapy

Individually titrate INFUMORPH to a dose that provides adequate analgesia and minimizes adverse reactions. Continually reevaluate patients receiving INFUMORPH to assess the maintenance of pain control, signs and symptoms of opioid withdrawal, and other adverse reactions, as well as to reassess for the development of addiction, abuse, or misuse [see Warnings and Precautions (5.3, 5.16)]. Frequent communication is important among the prescriber, other members of the healthcare team, the patient, and the caregiver/family during periods of changing analgesic requirements, including initial titration.

If the level of pain increases after dosage stabilization, attempt to identify the source of the increased pain before increasing the INFUMORPH dosage. If after increasing the dosage, unacceptable opioid-related adverse reactions are observed (including an increase in pain after a dosage increase), consider reducing the dosage [see Warnings and Precautions (5)]. Adjust the dosage to obtain an appropriate balance between management of pain and opioid-related adverse reactions.

Limited experience with continuous intrathecal infusion of morphine has shown that the daily doses have to be increased over time. Although the rate of increase, over time, in the dose required to sustain analgesia is highly variable, an estimate of the expected rate of increase is shown in the following Figure.

Doses above 20 mg/day should be employed with caution since they may be associated with a higher likelihood of serious side effects [see Warnings and Precautions (5.2,5.7) and Adverse Reactions (6)].

If unacceptable opioid-related adverse reactions are observed, consider reducing the dosage. Adjust the dosage to obtain an appropriate balance between management of pain and opioid-related adverse reactions.

2.6 Safe Reduction or Discontinuation of INFUMORPH

When a patient who has been taking INFUMORPH regularly and may be physically dependent or no longer requires therapy with INFUMORPH, taper the dose gradually while monitoring carefully for signs and symptoms of withdrawal. If the patient develops these signs or symptoms, raise the dose to the previous level and taper more slowly, either by increasing the interval between decreases, decreasing the amount of change in dose, or both. Do not rapidly reduce or abruptly discontinue INFUMORPH in patients who may be physically dependent on opioids [see Warnings and Precautions (5.15), Drug Abuse and Dependence (9.3)].

3 DOSAGE FORMS AND STRENGTHS

Injection: 200 mg per 20 mL (10 mg/mL) Preservative-free amber glass ampuls
Injection: 500 mg per 20 mL (25 mg/mL) Preservative-free amber glass ampuls

4 CONTRAINDICATIONS

INFUMORPH is contraindicated in patients with:

- Significant respiratory depression [see Warnings and Precautions (5.2)]
- Acute or severe bronchial asthma in an unmonitored setting or in the absence of resuscitative equipment [see Warnings and Precautions (5.9)]
- Concurrent use of monoamine oxidase inhibitors (MAOIs) or use of MAOIs within the last 14 days [see Warnings and Precautions (5.10), Drug Interactions (7)]
- Known or suspected gastrointestinal obstruction, including paralytic ileus [see Warnings and Precautions (5.14)]
- Hypersensitivity to morphine (e.g., anaphylaxis) [see Adverse Reactions (6)]

Neuraxial administration of INFUMORPH is contraindicated in patients with:

- Infection at the injection microinfusion site [see Warnings and Precautions (5.1)]
- Concomitant anticoagulant therapy [see Warnings and Precautions (5.1)]
- Uncontrolled bleeding diathesis [see Warnings and Precautions (5.1)]
- The presence of any other concomitant therapy or medical condition which would render epidural or intrathecal administration of medication especially hazardous.

5 WARNINGS AND PRECAUTIONS

5.1 Risks with Neuraxial Administration

Control of pain by neuraxial opiate delivery, using a continuous microinfusion device, is always accompanied by considerable risk to the patients and requires a high level of skill to be successfully accomplished. The task of treating these patients must be undertaken by experienced clinical teams, well-versed in patient selection, evolving technology and emerging standards of care.

INFUMORPH should be administered by or under the direction of a physician experienced in the techniques of epidural or intrathecal administration and familiar with the patient management problems associated with epidural or intrathecal drug administration. The physician should be familiar with patient conditions (such as infection at the injection site, bleeding diathesis, anticoagulant therapy, etc.) which call for special evaluation of the benefit versus risk potential.

Because of the risk of severe adverse effects when the epidural or intrathecal route of administration is employed, patients must be observed in a fully equipped and staffed environment for at least 24 hours after the initial dose.

The facility must be equipped to resuscitate patients with severe opioid overdosage, and the personnel must be familiar with the use and limitations of specific narcotic antagonists (naloxone, naltrexone) in such cases.

For safety reasons, it is recommended that administration of INFUMORPH 200 and 500 (10 and 25 mg/mL, respectively) by the intrathecal route be limited to the lumbar area.

5.2 Addiction, Abuse, and Misuse

INFUMORPH contains morphine, a Schedule II controlled substance. As an opioid, INFUMORPH exposes users to the risks of addiction, abuse, and misuse [see Drug Abuse and Dependence (9)].

Although the risk of addiction in any individual is unknown, it can occur in patients appropriately prescribed INFUMORPH. Addiction can occur at recommended dosages and if the drug is misused or abused. The risk of opioid-related overdose or overdose-related death is increased with higher opioid doses, and this risk persists over the course of therapy. In postmarketing studies, addiction, abuse, misuse, and fatal and non-fatal opioid overdose were observed in patients with long-term opioid use [see Adverse Reactions (6.2)].

Assess each patient’s risk for opioid addiction, abuse, or misuse prior to prescribing INFUMORPH, and monitor all patients receiving INFUMORPH for the development of these behaviors and conditions. Risks are increased in patients with a personal or family history of substance abuse (including drug or alcohol abuse or addiction) or mental illness (e.g., major depression). The potential for these risks should not, however, prevent the proper management of pain in any given patient.

Patients at increased risk may be prescribed opioids such as INFUMORPH but use in such patients necessitates intensive counseling about the risks and proper use of INFUMORPH along with intensive monitoring for signs of addiction, abuse, and misuse.

Opioids are sought for nonmedical use and are subject to diversion from legitimate prescribed use. Consider these risks when prescribing or dispensing INFUMORPH. Strategies to reduce these risks include prescribing the drug in the smallest appropriate quantity. Contact local state professional licensing board or state-controlled substances authority for information on how to prevent and detect abuse or diversion of this product.

Each ampul of INFUMORPH contains a large amount of a potent narcotic which has been associated with abuse and dependence among health care providers. Due to the limited indications for this product, the risk of overdosage and the risk of its diversion and abuse, it is recommended that special measures must be taken to control this product within the hospital or clinic. INFUMORPH should be subject to rigid accounting, rigorous control of wastage, and restricted access.

5.3 Life-Threatening Respiratory Depression

Serious, life-threatening, or fatal respiratory depression has been reported with the use of opioids, even when used as recommended. Respiratory depression, if not immediately recognized and treated, may lead to respiratory arrest and death. Management of respiratory depression may include close observation, supportive measures, and use of opioid overdose reversal agents (e.g., naloxone, nalmefene), depending on the patient’s clinical status [see Overdosage (10)]. Carbon dioxide (CO) retention from opioid-induced respiratory depression can exacerbate the sedating effects of opioids.

While serious, life-threatening, or fatal respiratory depression can occur at any time during the use of INFUMORPH, the risk is greatest during the initiation of therapy or following a dosage increase. This respiratory depression and/or respiratory arrest may be severe and could require intervention.

- Because of the risk of severe adverse effects, patients must be observed in a fully equipped and staffed environment for at least 24 hours after the initial (single) test dose and, as appropriate, for the first several days after catheter implantation. The facility must be equipped to resuscitate patients with severe opioid overdosage, and the personnel must be familiar with the use and limitations of specific narcotic antagonists (naloxone, naltrexone) in such cases
- Severe respiratory depression up to 24 hours following epidural or intrathecal administration has been reported.
- Intrathecal use has been associated with a higher incidence of respiratory depression than epidural use.
- Parenteral administration of narcotics in patients receiving epidural or intrathecal morphine may result in overdosage.

To reduce the risk of respiratory depression, proper dosing and titration of INFUMORPH are essential [see Dosage and Administration (2)]. Overestimating the INFUMORPH dosage when converting patients from another opioid product can result in a fatal overdose with the first dose.

IMPROPER OR ERRONEOUS SUBSTITUTION OF INFUMORPH 200 or 500 (10 or 25 mg/mL, respectively) FOR REGULAR DURAMORPH (0.5 or 1 mg/mL) IS LIKELY TO RESULT IN SERIOUS OVERDOSAGE, LEADING TO SEIZURES, RESPIRATORY DEPRESSION, AND DEATH.

Opioids can cause sleep-related breathing disorders including central sleep apnea (CSA) and sleep-related hypoxemia. Opioid use increases the risk of CSA in a dose-dependent fashion. In patients who present with CSA, consider decreasing the opioid dosage using best practices for opioid taper [seeDosage and Administration (2.6)].

5.4 Risks from Concomitant Use with Benzodiazepines or Other CNS Depressants

Profound sedation, respiratory depression, coma, and death may result from concomitant use of INFUMORPH with benzodiazepines and/or other CNS depressants, including alcohol (e.g., non-benzodiazepine sedatives/hypnotics, anxiolytics, tranquilizers, muscle relaxants, general anesthetics, antipsychotics, gabapentinoids [gabapentin or pregabalin], and other opioids). Because of these risks, reserve concomitant prescribing of these drugs for use in patients for whom alternative treatment options are inadequate.

Use of neuroleptics in conjunction with neuraxial morphine may increase the risk of respiratory depression.

Observational studies have demonstrated that concomitant use of opioid analgesics and benzodiazepines increases the risk of drug-related mortality compared to use of opioid analgesics alone. Because of similar pharmacological properties, it is reasonable to expect similar risk with the concomitant use of other CNS depressant drugs with opioid analgesics [see Drug Interactions (7)].

If the decision is made to prescribe a benzodiazepine or other CNS depressant concomitantly with an opioid analgesic, prescribe the lowest effective dosages and minimum durations of concomitant use. In patients already receiving an opioid analgesic, prescribe a lower initial dose of the benzodiazepine or other CNS depressant than indicated in the absence of an opioid, and titrate based on clinical response. If an opioid analgesic is initiated in a patient already taking a benzodiazepine or other CNS depressant, prescribe a lower initial dose of the opioid analgesic, and titrate based on clinical response. Monitor patients closely for signs and symptoms of respiratory depression and sedation.

5.5 Neonatal Opioid Withdrawal Syndrome

Use of INFUMORPH for an extended period of time during pregnancy can result in withdrawal in the neonate. Neonatal opioid withdrawal syndrome, unlike opioid withdrawal syndrome in adults, may be life-threatening if not recognized and treated, and requires management according to protocols developed by neonatology experts. Observe newborns for signs of neonatal opioid withdrawal syndrome and manage accordingly. Advise pregnant women using opioids for an extended period of time of the risk of neonatal opioid withdrawal syndrome and ensure that management by neonatology experts will be available at delivery [see Use in Specific Populations (8.1)].

5.6 Risk of Inflammatory Masses

Inflammatory masses such as granulomas, some of which have resulted in serious neurologic impairment including paralysis, have been reported to occur in patients receiving continuous infusion of opioid analgesics including INFUMORPH via indwelling intrathecal catheter. Patients receiving continuous infusion of INFUMORPH via indwelling intrathecal catheter should be carefully monitored for new neurologic signs or symptoms. Further assessment or intervention should be based on the clinical condition of the individual patient.

5.7 Risk of Tolerance and Myoclonic Activity

Patients sometimes manifest unusual acceleration of neuraxial morphine requirements, which may cause concern regarding systemic absorption and the hazards of large doses; these patients may benefit from hospitalization and detoxification. Two cases of myoclonic-like spasm of the lower extremities have been reported in patients receiving more than 20 mg/day of intrathecal morphine. After detoxification, it might be possible to resume treatment at lower doses, and some patients have been successfully changed from continuous epidural morphine to continuous intrathecal morphine. Repeat detoxification may be indicated at a later date. The upper daily dosage limit for each patient during continuing treatment must be individualized.

5.8 Opioid-Induced Hyperalgesia and Allodynia

Opioid-Induced Hyperalgesia (OIH) occurs when an opioid analgesic paradoxically causes an increase in pain, or an increase in sensitivity to pain. This condition differs from tolerance, which is the need for increasing doses of opioids to maintain a defined effect [see Dependence (9.3)]. Symptoms of OIH include (but may not be limited to) increased levels of pain upon opioid dosage increase, decreased levels of pain upon opioid dosage decrease, or pain from ordinarily non-painful stimuli (allodynia). These symptoms may suggest OIH only if there is no evidence of underlying disease progression, opioid tolerance, opioid withdrawal, or addictive behavior.

Cases of OIH have been reported, both with short-term and longer-term use of opioid analgesics. Though the mechanism of OIH is not fully understood, multiple biochemical pathways have been implicated. Medical literature suggests a strong biologic plausibility between opioid analgesics and OIH and allodynia. If a patient is suspected to be experiencing OIH, carefully consider appropriately decreasing the dose of the current opioid analgesic, or opioid rotation (safety switching the patient to a different opioid moiety) [see Dosage and Administration (2), Warnings and Precautions (5.16)].

5.9 Life-Threatening Respiratory Depression in Patients with Chronic Pulmonary Disease or in Elderly, Cachectic, or Debilitated Patients

The use of INFUMORPH in patients with acute or severe bronchial asthma in an unmonitored setting or in the absence of resuscitative equipment is contraindicated.

Patients with Chronic Pulmonary Disease: Patients with significant chronic obstructive pulmonary disease or cor pulmonale, and those with a substantially decreased respiratory reserve, hypoxia, hypercapnia, or pre-existing respiratory depression are at increased risk of decreased respiratory drive including apnea, even at recommended doses of INFUMORPH [see Warnings and Precautions (5.3)].

Elderly, Cachectic, or Debilitated Patients: Life-threatening respiratory depression is more likely to occur in elderly, cachectic, or debilitated patients because they may have altered pharmacokinetics or altered clearance compared to younger, healthier patients [see Warnings and Precautions (5.3)].

Monitor such patients closely, particularly when initiating and titrating INFUMORPH and when INFUMORPH is given concomitantly with other drugs that depress respiration [see Warnings and Precautions (5.3, 5.4), Drug Interactions (7)]. Alternatively, consider the use of non-opioid analgesics in these patients.

5.10 Interaction with Monoamine Oxidase Inhibitors

Monoamine oxidase inhibitors (MAOIs) may potentiate the effects of morphine, including respiratory depression, coma, and confusion. Morphine Sulfate Injection should not be used in patients taking MAOIs or within 14 days of stopping such treatment [see Drug Interactions (7)].

5.11 Adrenal Insufficiency

Cases of adrenal insufficiency have been reported with opioid use, more often following greater than one month of use. Presentation of adrenal insufficiency may include nonspecific symptoms and signs including nausea, vomiting, anorexia, fatigue, weakness, dizziness, and low blood pressure. If adrenal insufficiency is suspected, confirm the diagnosis with diagnostic testing as soon as possible. If adrenal insufficiency is diagnosed, treat with physiologic replacement doses of corticosteroids. Wean the patient off of the opioid to allow adrenal function to recover and continue corticosteroid treatment until adrenal function recovers. Other opioids may be tried as some cases reported use of a different opioid without recurrence of adrenal insufficiency. The information available does not identify any particular opioids as being more likely to be associated with adrenal insufficiency.

5.12 Severe Hypotension

INFUMORPH may cause severe hypotension including orthostatic hypotension and syncope in ambulatory patients. There is increased risk in patients whose ability to maintain blood pressure has already been compromised by a reduced blood volume or concurrent administration of certain CNS depressant drugs (e.g., phenothiazines or general anesthetics) [see Drug Interactions (7)]. Monitor these patients for signs of hypotension after initiating or titrating the dosage of INFUMORPH. In patients with circulatory shock, INFUMORPH may cause vasodilation that can further reduce cardiac output and blood pressure. Avoid the use of INFUMORPH in patients with circulatory shock.

5.13 Risks of Use in Patients with Increased Intracranial Pressure, Brain Tumors, Head Injury, or Impaired Consciousness

In patients who may be susceptible to the intracranial effects of CO retention (e.g., those with evidence of increased intracranial pressure or brain tumors), INFUMORPH may reduce respiratory drive, and the resultant CO retention can further increase intracranial pressure. Monitor such patients for signs of sedation and respiratory depression, particularly when initiating therapy with INFUMORPH. INFUMORPH should be used with extreme caution in patients with head injury or increased intracranial pressure. Pupillary changes (miosis) from morphine may obscure the existence, extent and course of intracranial pathology. High doses of neuraxial morphine may produce myoclonic events [see Warnings and Precautions (5.7)]. Clinicians should maintain a high index of suspicion for adverse drug reactions when evaluating altered mental status or movement abnormalities in patients receiving this modality of treatment.

Opioids may also obscure the clinical course in a patient with a head injury. Avoid the use of INFUMORPH in patients with impaired consciousness or coma.

5.14 Risks of Gastrointestinal Complications

INFUMORPH is contraindicated in patients with known or suspected gastrointestinal obstruction, including paralytic ileus.

The morphine in INFUMORPH may cause spasm of the sphincter of Oddi. Opioids may cause increases in serum amylase. Monitor patients with biliary tract disease, including acute pancreatitis for worsening symptoms. As significant morphine is released into the systemic circulation from neuraxial administration, the ensuing smooth muscle hypertonicity may result in biliary colic.

Cases of opioid-induced esophageal dysfunction (OIED) have been reported in patients taking opioids. The risk of OIED may increase as the dose and/or duration of opioids increases. Regularly evaluate patients for signs and symptoms of OIED (e.g., dysphagia, regurgitation, non-cardiac chest pain) and, if necessary, adjust opioid therapy as clinically appropriate [see Clinical Pharmacology (12.2)].

5.15 Increased Risk of Seizures in Patients with Seizure Disorders

The morphine in INFUMORPH may increase the frequency of seizures in patients with seizure disorders, and may increase the risk of seizures occurring in other clinical setting associated with seizures. Monitor patients with a history of seizure disorders for worsened seizure control during INFUMORPH therapy.

5.16 Withdrawal

Avoid the use of mixed agonist/antagonist (e.g., pentazocine, nalbuphine, and butorphanol) or partial agonist (e.g., buprenorphine) analgesics in patients who are receiving a full opioid agonist analgesic, including INFUMORPH. In these patients, mixed agonist/antagonist and partial agonist analgesics may reduce the analgesic effect and/or precipitate withdrawal symptoms [see Drug Interactions (7)].

When discontinuing INFUMORPH, gradually taper the dosage [see Dosage and Administration (2.6)]. Do not rapidly reduce or abruptly discontinue INFUMORPH [see Drug Abuse and Dependence (9.3)].

5.17 Risks of Driving and Operating Machinery

INFUMORPH may impair the mental or physical abilities needed to perform potentially hazardous activities such as driving a car or operating machinery. Warn patients not to drive or operate dangerous machinery unless they are tolerant to the effects of INFUMORPH and know how they will react to the medication.

5.18 Risks of Use in Patients with Urinary System Disorders

Urinary retention, which may persist 10 to 20 hours following single epidural or intrathecal administration, is frequently associated with neuraxial opioid administration and must be anticipated, more frequently in male patients than female patients. Urinary retention may also occur during the first several days of hospitalization for the initiation of continuous intrathecal or epidural morphine therapy. Early recognition of difficulty in urination and prompt intervention in cases of urinary retention is indicated. Patients who develop urinary retention have responded to cholinomimetic treatment and/or judicious use of catheters.

5.19 Risks of Use in Ambulatory Patients

Patients with reduced circulating blood volume, impaired myocardial function or on sympatholytic drugs should be monitored for the possible occurrence of orthostatic hypotension, a frequent complication in single-dose neuraxial morphine analgesia.

6 ADVERSE REACTIONS

The following serious adverse reactions are described, or described in greater detail, in other sections:

- Addiction, Abuse, and Misuse [see Warnings and Precautions (5.2)]
- Life-Threatening Respiratory Depression [see Warnings and Precautions (5.3)]
- Interactions with CNS Benzodiazepines or Other Depressants [see Warnings and Precautions (5.4)]
- Neonatal Opioid Withdrawal Syndrome [see Warnings and Precautions (5.5)]
- Inflammatory Masses [see Warnings and Precautions (5.6)]
- Myoclonic Activity [see Warnings and Precautions (5.7)]
- Opioid-Induced Hyperalgesia and Allodynia [see Warnings and Precautions (5.8)]
- Adrenal Insufficiency [see Warnings and Precautions (5.11)]
- Severe Hypotension [see Warnings and Precautions (5.12)]
- Gastrointestinal Adverse Reactions [see Warnings and Precautions (5.14)]
- Seizures [see Warnings and Precautions (5.15)]
- Withdrawal [see Warnings and Precautions (5.16)]
- Urinary Retention [see Warnings and Precautions (5.18)]
- Orthostatic Hypotension [see Warnings and Precautions (5.19)]

The following adverse reactions associated with the use of morphine were identified in clinical studies or postmarketing reports. Because some of these reactions were reported voluntarily from a population of uncertain size, it is not always possible to reliably estimate their frequency or establish a causal relationship to drug exposure.

The most serious adverse reactions encountered during continuous intrathecal or epidural infusion of INFUMORPH were respiratory depression, myoclonus, and formation of inflammatory masses.

Cardiovascular System: While low doses of intravenously administered morphine have little effect on cardiovascular stability, high doses are excitatory, resulting from sympathetic hyperactivity and increase in circulating catecholamines. Excitation of the central nervous system, resulting in convulsions, may accompany high doses of morphine given intravenously.

Central Nervous System: myoclonus, seizures, dysphoric reactions, toxic psychosis, dizziness, euphoria, anxiety, confusion, headache. Lumbar puncture-type headache is encountered in a significant minority of cases for several days following intrathecal catheter implantation and generally responds to bed rest and/or other conventional therapy.

Gastrointestinal System: Nausea, vomiting, constipation

Skin: Pruritus, urticaria, wheals, and/or local tissue irritation.

Genito-Urinary System: Urinary retention, oliguria, unexplained genital swelling in male patients, following infusion-device implant surgery.

Other: Other adverse experiences reported following morphine therapy include depression of cough reflex, interference with thermal regulation, peripheral edema.

Serotonin syndrome: Cases of serotonin syndrome, a potentially life-threatening condition, have been reported during concomitant use of opioids with serotonergic drugs.

Adrenal insufficiency: Cases of adrenal insufficiency have been reported with opioid use, more often following greater than one month of use.

Anaphylaxis: Anaphylaxis has been reported with ingredients contained in INFUMORPH.

Androgen deficiency: Cases of androgen deficiency have occurred with use of opioids for an extended period of time. [see Clinical Pharmacology (12.2)].

Hyperalgesia and Allodynia: Cases of hyperalgesia and allodynia have been reported with opioid therapy of any duration [see Warnings and Precautions (5.8)]

Hypoglycemia: Cases of hypoglycemia have been reported in patients taking opioids. Most reports were in patients with at least one predisposing risk factor (e.g., diabetes).

Opioid-induced esophageal dysfunction (OIED): Cases of OIED have been reported in patients taking opioids and may occur more frequently in patients taking higher doses of opioids, and/or in patients taking opioids longer term [see Warnings and Precautions (5.14)].

Adverse Reactions from Observational Studies

A prospective, observational cohort study estimated the risks of addiction, abuse, and misuse in patients initiating long-term use of Schedule II opioid analgesics between 2017 and 2021. Study participants included in one or more analyses had been enrolled in selected insurance plans or health systems for at least one year, were free of at least one outcome at baseline, completed a minimum number of follow-up assessments, and either: 1) filled multiple extended-release/long-acting opioid analgesic prescriptions during a 90-day period (n=978); or 2) filled any Schedule II opioid analgesic prescriptions covering at least 70 of 90 days (n=1,244). Those included also had no dispensing of the qualifying opioids in the previous 6 months.

Over 12 months:

- approximately 1% to 6% of participants across the two cohorts newly met criteria for addiction, as assessed with two validated interview-based measures of moderate-to-severe opioid use disorder based on Diagnostic and Statistical Manual of Mental Disorders, Fifth Edition (DSM-5) criteria, and
- approximately 9% and 22% of participants across the two cohorts newly met criteria for prescription opioid abuse and misuse [defined in Drug Abuse and Dependence (9.2)], respectively, as measured with a validated self-reported instrument.

A retrospective, observational cohort study estimated the risk of opioid-involved overdose or opioid overdose-related death in patients with new long-term use of Schedule II opioid analgesics from 2006 through 2016 (n=220,249). Included patients had been enrolled in either one of two commercial insurance programs, one managed care program, or one Medicaid program for at least 9 months. New long-term use was defined as having Schedule II opioid analgesic prescriptions covering at least 70 days’ supply over the 3 months prior to study entry and none during the preceding 6 months. Patients were excluded if they had an opioid-involved overdose in the 9 months prior to study entry. Overdose was measured using a validated medical code-based algorithm with linkage to the National Death Index database. The 5-year cumulative incidence estimates for opioid-involved overdose or opioid overdose-related death ranged from approximately 1.5% to 4% across study sites, counting only the first event during follow-up. Approximately 17% of first opioid overdoses observed over the entire study period (5-11 years, depending on the study site) were fatal. Higher baseline opioid dose was the strongest and most consistent predictor of opioid-involved overdose or opioid overdose-related death. Study exclusion criteria may have selected patients at lower risk of overdose, and substantial loss to follow-up (approximately 80%) also may have biased estimates.

The risk estimates from the studies described above may not be generalizable to all patients receiving opioid analgesics, such as those with exposures shorter or longer than the duration evaluated in the studies.

7 DRUG INTERACTIONS

Table 1 includes clinically significant drug interactions with INFUMORPH.

Table 1. Clinically Significant Drug Interactions with INFUMORPH

Benzodiazepines and Other Central Nervous System (CNS) Depressants
Clinical Impact: | Due to additive pharmacologic effect, the concomitant use of benzodiazepines or other CNS depressants, including alcohol, can increase the risk of hypotension, respiratory depression, profound sedation, coma, and death. The depressant effects of morphine are potentiated by the presence of other CNS depressants. Use of neuroleptics in conjunction with neuraxial morphine may increase the risk of respiratory depression [see Warnings and Precautions (5.4)].
Intervention: | Reserve concomitant prescribing of these drugs for use in patients for whom alternative treatment options are inadequate. Limit dosages and durations to the minimum required. Monitor patients closely for signs of respiratory depression and sedation [see Warnings and Precautions (5.4)].
Examples: | Benzodiazepines and other sedatives/hypnotics, anxiolytics, tranquilizers, muscle relaxants, general anesthetics, antipsychotics, psychotropic drugs, antihistamines, neuroleptics, gabapentinoids (gabapentin or pregabalin), other opioids, alcohol.
Serotonergic Drugs
Clinical Impact: | The concomitant use of opioids with other drugs that affect the serotonergic neurotransmitter system has resulted in serotonin syndrome.
Intervention: | If concomitant use is warranted, carefully observe the patient, particularly during treatment initiation and dose adjustment. Discontinue INFUMORPH if serotonin syndrome is suspected.
Examples: | Selective serotonin reuptake inhibitors (SSRIs), serotonin and norepinephrine reuptake inhibitors (SNRIs), tricyclic antidepressants (TCAs), triptans, 5-HT3 receptor antagonists, drugs that effect the serotonin neurotransmitter system (e.g., mirtazapine, trazodone, tramadol), certain muscle relaxants (i.e., cyclobenzaprine, metaxalone), monoamine oxidase inhibitors (those intended to treat psychiatric disorders and also others, such as linezolid and intravenous methylene blue).
Monoamine Oxidase Inhibitors (MAOIs)
Clinical Impact: | MAOI interactions with opioids may manifest as serotonin syndrome or opioid toxicity (e.g., respiratory depression, coma) [see Warnings and Precautions (5.10)].
Intervention: | Do not use INFUMORPH in patients taking MAOIs or within 14 days of stopping such treatment. If urgent use of an opioid is necessary, use test doses and frequent titration of small doses of other opioids (such as oxycodone, hydromorphone, oxymorphone, hydrocodone, or buprenorphine) to treat pain while closely monitoring blood pressure and signs and symptoms of CNS and respiratory depression.
Examples: | phenelzine, tranylcypromine, linezolid
Mixed Agonist/Antagonist and Partial Agonist Opioid Analgesics
Clinical Impact: | May reduce the analgesic effect of INFUMORPH and/or precipitate withdrawal symptoms.
Intervention: | Avoid concomitant use.
Examples: | Butorphanol, nalbuphine, pentazocine, buprenorphine.
Muscle Relaxants
Clinical Impact: | Morphine may enhance the neuromuscular blocking action of skeletal muscle relaxants and produce an increased degree of respiratory depression.
Intervention: | Monitor patients for signs of respiratory depression that may be greater than otherwise expected and decrease the dosage of INFUMORPH and/or the muscle relaxant as necessary.
Examples: | Cyclobenzaprine, metaxalone.
Diuretics
Clinical Impact: | Opioids can reduce the efficacy of diuretics by inducing the release of antidiuretic hormone.
Intervention: | Monitor patients for signs of diminished diuresis and/or effects on blood pressure and increase the dosage of the diuretic as needed.
Anticholinergic Drugs
Clinical Impact: | The concomitant use of anticholinergic drugs may increase risk of urinary retention and/or severe constipation, which may lead to paralytic ileus.
Intervention: | Monitor patients for signs of urinary retention or reduced gastric motility when INFUMORPH is used concomitantly with anticholinergic drugs.
Oral P2Y12 Inhibitors
Clinical Impact: | The co-administration of oral P2Y12 inhibitors and intravenous morphine sulfate can decrease the absorption and peak concentration of oral P2Y12 inhibitors and delay the onset of the antiplatelet effect.
Intervention: | Consider the use of parenteral antiplatelet agent in the setting of acute coronary syndrome requiring co-administration of intravenous morphine sulfate.
Examples: | clopidogrel, prasugrel, ticagrelor

8 USE IN SPECIFIC POPULATIONS

8.1 Pregnancy

Risk Summary

Use of opioid analgesics for an extended period of time during pregnancy may cause neonatal opioid withdrawal syndrome [see Warnings and Precautions (5.5)]. Available data with INFUMORPH in pregnant women are insufficient to inform a drug-associated risk for major birth defects and miscarriage. There are adverse outcomes reported with fetal exposure to opioid analgesics (see Clinical Considerations). Published studies with morphine use during pregnancy have not reported a clear association with morphine and major birth defects [see Human Data]. In published animal reproduction studies, morphine administered subcutaneously during the early gestational period produced neural tube defects (i.e., exencephaly and cranioschisis) at 5 and 16 times the human daily dose of 60 mg based on body surface area (HDD) in hamsters and mice, respectively, lower fetal body weight and increased incidence of abortion at 0.4 times the HDD in the rabbit, growth retardation at 6 times the HDD in the rat, and axial skeletal fusion and cryptorchidism at 16 times the HDD in the mouse. Administration of morphine sulfate to pregnant rats during organogenesis and through lactation resulted in cyanosis, hypothermia, decreased brain weights, pup mortality, decreased pup body weights, and adverse effects on reproductive tissues at 3-4 times the HDD; and long-term neurochemical changes in the brain of offspring which correlate with altered behavioral responses that persist through adulthood at exposures comparable to and less than the HDD [see Animal Data]. Based on animal data, advise pregnant women of the potential risk to a fetus.
The background risk of major birth defects and miscarriage for the indicated population is unknown.
All pregnancies have a background risk of birth defect, loss, or other adverse outcomes. In the U.S. general population, the estimated background risk of major birth defects and miscarriage in clinically recognized pregnancies is 2 to 4% and 15 to 20%, respectively.
Clinical Considerations
Fetal/Neonatal Adverse Reactions
Use of opioid analgesics for an extended period of time during pregnancy for medical or nonmedical purposes can result in physical dependence in the neonate and neonatal opioid withdrawal syndrome shortly after birth.
Neonatal opioid withdrawal syndrome presents as irritability, hyperactivity and abnormal sleep pattern, high pitched cry, tremor, vomiting, diarrhea, and failure to gain weight. The onset, duration, and severity of neonatal opioid withdrawal syndrome vary based on the specific opioid used, duration of use, timing and amount of last maternal use, and rate of elimination of the drug by the newborn.
Observe newborns for symptoms of neonatal opioid withdrawal syndrome and manage accordingly [see Warnings and Precautions (5.5)].
Labor or Delivery
INFUMORPH 200 and 500 (10 and 25 mg/mL, respectively) are too highly concentrated for routine use in obstetric neuraxial analgesia. Opioids, including intravenously, epidurally, and intrathecally administered morphine, readily cross the placenta and may produce respiratory depression and psycho-physiologic effects in neonates. An opioid antagonist, such as naloxone, and resuscitative equipment must be available for reversal of opioid-induced respiratory depression in the neonate.
INFUMORPH is not recommended for use in pregnant women during or immediately prior to labor, when other analgesic techniques are more appropriate. Opioid analgesics, including INFUMORPH, can prolong labor through actions which temporarily reduce the strength, duration, and frequency of uterine contractions. However, this effect is not consistent and may be offset by an increased rate of cervical dilation, which tends to shorten labor. Monitor neonates exposed to opioid analgesics during labor for signs of excess sedation and respiratory depression.
Data
Human Data
The results from a population-based prospective cohort, including 70 women exposed to morphine during the first trimester of pregnancy and 448 women exposed to morphine at any time during pregnancy, indicate no increased risk for congenital malformations. However, these studies cannot definitely establish the absence of any risk because of methodological limitations, including small sample size and nonrandomized study design.
Animal Data
Formal reproductive and developmental toxicology studies for morphine have not been conducted. Exposure margins for the following published study reports are based on human daily dose of 60 mg morphine using a body surface area comparison (HDD).
Neural tube defects (exencephaly and cranioschisis) were noted following subcutaneous administration of morphine sulfate (35-322 mg/kg) on Gestation Day 8 to pregnant hamsters (4.7 to 43.5 times the HDD). A no adverse effect level was not defined in this study and the findings cannot be clearly attributed to maternal toxicity. Neural tube defects (exencephaly), axial skeletal fusions, and cryptorchidism were reported following a single subcutaneous (SC) injection of morphine sulfate to pregnant mice (100-500 mg/kg) on Gestation Day 8 or 9 at 200 mg/kg or greater (16 times the HDD) and fetal resorption at 400 mg/kg or higher (32 times the HDD). No adverse effects were noted following 100 mg/kg morphine in this model (8 times the HDD). In one study, following continuous subcutaneous infusion of doses greater than or equal to 2.72 mg/kg to mice (0.2 times the HDD), exencephaly, hydronephrosis, intestinal hemorrhage, split supraoccipital, malformed sternebrae, and malformed xiphoid were noted. The effects were reduced with increasing daily dose; possibly due to rapid induction of tolerance under these infusion conditions. The clinical significance of this report is not clear.
Decreased fetal weights were observed in pregnant rats treated with 20 mg/kg/day morphine sulfate (3.2 times the HDD) from Gestation Day 7 to 9. There was no evidence of malformations despite maternal toxicity (10% mortality). In a second rat study, decreased fetal weight and increased incidences of growth retardation were noted at 35 mg/kg/day (5.7 times the HDD) and there was a reduced number of fetuses at 70 mg/kg/day (11.4 times the HDD) when pregnant rats were treated with 10, 35, or 70 mg/kg/day morphine sulfate via continuous infusion from Gestation Day 5 to 20.
There was no evidence of fetal malformations or maternal toxicity.
An increased incidence of abortion was noted in a study in which pregnant rabbits were treated with 2.5 (0.8 times the HDD) to 10 mg/kg morphine sulfate via subcutaneous injection from Gestation Day 6 to 10. In a second study, decreased fetal body weights were reported following treatment of pregnant rabbits with increasing doses of morphine (10-50 mg/kg/day) during the pre-mating period and 50 mg/kg/day (16 times the HDD) throughout the gestation period. No overt malformations were reported in either publication; although only limited endpoints were evaluated.

In published studies in rats, exposure to morphine during gestation and/or lactation periods is associated with: decreased pup viability at 12.5 mg/kg/day or greater (2 times the HDD); decreased pup body weights at 15 mg/kg/day or greater (2.4 times the HDD); decreased litter size, decreased absolute brain and cerebellar weights, cyanosis, and hypothermia at 20 mg/kg/day (3.2 times the HDD); alteration of behavioral responses (play, social-interaction) at 1 mg/kg/day or greater (0.2 times the HDD); alteration of maternal behaviors (e.g., decreased nursing and pup retrievals) in mice at 1 mg/kg or higher (0.08 times the HDD) and rats at 1.5 mg/kg/day or higher (0.2 times the HDD); and a host of behavioral abnormalities in the offspring of rats, including altered responsiveness to opioids at 4 mg/kg/day (0.7 times the HDD) or greater.
Fetal and/or postnatal exposure to morphine in mice and rats has been shown to result in morphological changes in fetal and neonatal brain and neuronal cell loss, alteration of a number of neurotransmitter and neuromodulator systems, including opioid and nonopioid systems, and impairment in various learning and memory tests that appear to persist into adulthood. These studies were conducted with morphine treatment usually in the range of 4 to 20 mg/kg/day (0.7 to 3.2 times the HDD).
Additionally, delayed sexual maturation and decreased sexual behaviors in female offspring at 20 mg/kg/day (3.2 times the HDD), and decreased plasma and testicular levels of luteinizing hormone and testosterone, decreased testes weights, seminiferous tubule shrinkage, germinal cell aplasia, and decreased spermatogenesis in male offspring were also observed at 20 mg/kg/day (3.2 times the HDD). Decreased litter size and viability were observed in the offspring of male rats that were intraperitoneally administered morphine sulfate for 1 day prior to mating at 25 mg/kg/day (4.1 times the HDD) and mated to untreated females. Decreased viability and body weight and/or movement deficits in both first and second generation offspring were reported when male mice were treated for 5 days with escalating doses of 120 to 240 mg/kg/day morphine sulfate (9.7 to 19.5 times the HDD) or when female mice treated with escalating doses of 60 to 240 mg/kg/day (4.9 to 19.5 times the HDD) followed by a 5-day treatment-free recovery period prior to mating. Similar multigenerational findings were also seen in female rats pre-gestationally treated with escalating doses of 10 to 22 mg/kg/day morphine (1.6 to 3.6 times the HDD).

8.2 Lactation

Risk Summary
Morphine is present in breast milk. Published lactation studies report variable concentrations of morphine in breast milk with administration of immediate-release morphine to nursing mothers in the early postpartum period with a milk-to-plasma morphine AUC ratio of 2.5:1 measured in one lactation study. However, there is insufficient information to determine the effects of morphine on the breastfed infant and the effects of morphine on milk production. Lactation studies have not been conducted with INFUMORPH, and no information is available on the effects of the drug on the breastfed infant or the effects of the drug on milk production.
The developmental and health benefits of breastfeeding should be considered along with the mother’s clinical need for INFUMORPH and any potential adverse effects on the breastfed infant from INFUMORPH or from the underlying maternal condition.
Clinical Considerations
Monitor infants exposed to INFUMORPH through breast milk for excess sedation and respiratory depression. Withdrawal symptoms can occur in breastfed infants when maternal administration of morphine is stopped, or when breastfeeding is stopped.

8.3 Females and Males of Reproductive Potential

Infertility
Use of opioids for an extended period of time may cause reduced fertility in females and males of reproductive potential. It is not known whether these effects on fertility are reversible [see Adverse Reactions (6), Clinical Pharmacology (12.2)].
In published animal studies, morphine administration adversely effected fertility and reproductive endpoints in male rats and prolonged estrus cycle in female rats [see Nonclinical Toxicology (13)].

8.4 Pediatric Use

Adequate studies to establish the safety and effectiveness of spinal morphine in pediatric patients have not been performed, and usage in this population is not recommended.

8.5 Geriatric Use

Elderly patients (aged 65 years or older) may have increased sensitivity to INFUMORPH. In general, use caution when selecting a dosage for an elderly patient, usually starting at the low end of the dosing range, reflecting the greater frequency of decreased hepatic, renal, or cardiac function and of concomitant disease or other drug therapy.
Respiratory depression is the chief risk for elderly patients treated with opioids, and has occurred after large initial doses were administered to patients who were not opioid tolerant or when opioids were co-administered with other agents that depress respiration. Titrate the dosage of INFUMORPH slowly in geriatric patients and monitor closely for signs of central nervous system and respiratory depression [see Warnings and Precautions (5.8)].
The pharmacodynamic effects of neuraxial morphine in the elderly are more variable than in the younger population. Patients will vary widely in the effective initial dose, rate of development of tolerance and the frequency and magnitude of associated adverse effects as the dose is increased.
Initial doses should be based on careful clinical observation following “test doses”, after making due allowances for the effects of the patient’s age and infirmity on his/her ability to clear the drug, particularly in patients receiving epidural morphine.
Morphine is known to be substantially excreted by the kidney, and the risk of adverse reactions to this drug may be greater in patients with impaired renal function. Because elderly patients are more likely to have decreased renal function, care should be taken in dose selection, and it may be useful to monitor renal function.

8.6 Hepatic or Renal Impairment

The elimination half-life of morphine may be prolonged in patients with reduced metabolic rates and with hepatic and/or renal dysfunction. Hence, care should be exercised in administering INFUMORPH epidurally to patients with these conditions. High blood morphine levels, due to reduced clearance, may take several days to develop.

9 DRUG ABUSE AND DEPENDENCE

9.1 Controlled Substance

INFUMORPH contains morphine, a Schedule II controlled drug substance.

9.2 Abuse

INFUMORPH contains morphine, a substance with high potential for misuse and abuse, which can lead to the development of substance use disorder, including addiction [see Warnings and Precautions (5.2)].

Misuse is the intentional use, for therapeutic purposes, of a drug by an individual in a way other than prescribed by a healthcare provider or for whom it was not prescribed. Abuse is the intentional, non- therapeutic use of a drug, even once, for its desirable psychological or physiological effects.

Drug addiction is a cluster of behavioral, cognitive, and physiological phenomena that may include a strong desire to take the drug, difficulties in controlling drug use (e.g., continuing drug use despite harmful consequences, giving a higher priority to drug use than other activities and obligations), and possible tolerance or physical dependence.

Misuse and abuse of INFUMORPH increases risk of overdose, which may lead to central nervous system and respiratory depression, hypotension, seizures, and death. The risk is increased with concurrent abuse of INFUMORPH with alcohol and/or other CNS depressants.

Abuse of and addiction to opioids in some individuals may not be accompanied by concurrent tolerance and symptoms of physical dependence. In addition, abuse of opioids can occur in the absence of addiction.

All patients treated with opioids require careful and frequent reevaluation for signs of misuse, abuse, and addiction, because use of opioid analgesic products carries the risk of addiction even under appropriate medical use. Patients at high risk of INFUMORPH abuse include those with a history of prolonged use of any opioid, including products containing morphine, those with a history of drug or alcohol abuse, or those who use INFUMORPH in combination with other abused drugs.

“Drug-seeking” behavior is very common in persons with substance use disorders. Drug-seeking tactics include emergency calls or visits near the end of office hours, refusal to undergo appropriate examination, testing, or referral, repeated “loss” of prescriptions, tampering with prescriptions, and reluctance to provide prior medical records or contact information for other treating healthcare provider(s). “Doctor shopping” (visiting multiple prescribers to obtain additional prescriptions) is common among people who abuse drugs and people with substance use disorder. Preoccupation with achieving adequate pain relief can be appropriate behavior in a patient with inadequate pain control.

INFUMORPH, like other opioids, can be diverted for nonmedical use into illicit channels of distribution. Careful recordkeeping of prescribing information, including quantity, frequency, and renewal requests, as required by state and federal law, is strongly advised.

Proper assessment of the patient, proper prescribing practices, periodic reevaluation of therapy, and proper dispensing and storage are appropriate measures that help to limit abuse of opioid drugs.

Risks Specific to Abuse of INFUMORPH

Abuse of INFUMORPH poses a risk of overdose and death. The risk is increased with concurrent use of INFUMORPH with alcohol and/or other CNS depressants.

Parenteral drug abuse is commonly associated with transmission of infectious diseases such as hepatitis and HIV.

9.3 Dependence

Both tolerance and physical dependence can develop during use of opioid therapy.

Tolerance is a physiological state characterized by a reduced response to a drug after repeated administration (i.e., a higher dose of a drug is required to produce the same effect that was once obtained at a lower dose).

Physical dependence is a state that develops as a result of a physiological adaptation in response to repeated drug use, manifested by withdrawal signs and symptoms after abrupt discontinuation or a significant dose reduction of a drug.

Withdrawal may be precipitated through the administration of drugs with opioid antagonist activity (e.g., naloxone), mixed agonist/antagonist analgesics (e.g., pentazocine, butorphanol, nalbuphine), or partial agonists (e.g., buprenorphine). Physical dependence may not occur to a clinically significant degree until after several days to weeks of continued use.

INFUMORPH should not be abruptly discontinued in a physically-dependent patient [see Dosage and Administration (2.6)]. If INFUMORPH is abruptly discontinued in a physically-dependent patient, a withdrawal syndrome may occur, typically characterized by restlessness, lacrimation, rhinorrhea, perspiration, chills, myalgia, and mydriasis. Other signs and symptoms also may develop, including irritability, anxiety, backache, joint pain, weakness, abdominal cramps, insomnia, nausea, anorexia, vomiting, diarrhea, or increased blood pressure, respiratory rate, or heart rate.

Infants born to mothers physically dependent on opioids will also be physically dependent and may exhibit respiratory difficulties and withdrawal signs [see Use in Specific Populations (8.1)].

10 OVERDOSAGE

Clinical Presentation

Acute overdose with INFUMORPH can be manifested by respiratory depression, somnolence progressing to stupor or coma, skeletal muscle flaccidity, cold and clammy skin, constricted pupils, and, in some cases, pulmonary edema, bradycardia, hypotension, hypoglycemia, partial or complete airway obstruction, atypical snoring, and death. Marked mydriasis rather than miosis may be seen with hypoxia in overdose situations [see Clinical Pharmacology (12.2)]. Toxic leukoencephalopathy has been reported after opioid overdose and can present hours, days, or weeks after apparent recovery from the initial intoxication.

Treatment of Overdose

In case of overdose, priorities are the reestablishment of a patent and protected airway and institution of assisted or controlled ventilation, if needed. Employ other supportive measures (including oxygen and vasopressors) in the management of circulatory shock and pulmonary edema as indicated.

Cardiac arrest or arrhythmias will require advanced life-support measures.

For clinically significant respiratory or circulatory depression secondary to morphine overdose, administer an opioid overdose reversal agent such as naloxone or nalmefene.

As the duration of effect of naloxone is considerably shorter than that of epidural or intrathecal morphine, repeated administration may be necessary. Patients should be closely observed for evidence of renarcotization.

Because the duration of opioid reversal is expected to be less than the duration of action of morphine in INFUMORPH, particularly with epidural or intrathecal morphine, carefully monitor the patient until spontaneous respiration is reliably re-established. If the response to an opioid overdose reversal agent is suboptimal or only brief in nature, administer additional reversal agent as directed by the product’s prescribing information.

In an individual physically dependent on opioids, administration of the recommended usual dosage of the opioid reversal agent will precipitate an acute withdrawal syndrome. The severity of the withdrawal symptoms experienced will depend on the degree of physical dependence and the dose of the reversal agent administered. If a decision is made to treat serious respiratory depression in the physically-dependent patient, administration of the reversal agent should be begun with care and by titration with smaller than usual doses of the reversal agent.

11 DESCRIPTION

INFUMORPH (preservative-free morphine sulfate sterile solution) is an opioid agonist, available as a sterile, nonpyrogenic, isobaric, high potency solution of morphine sulfate in strengths of 10 mg or 25 mg morphine sulfate per mL, free of antioxidants, preservatives or other potentially neurotoxic additives. INFUMORPH is intended for use in continuous microinfusion devices for intraspinal administration in the management of pain. Morphine is the most important alkaloid of opium and is a phenanthrene derivative. It is available as the sulfate salt, chemically identified as 7,8-Didehydro-4,5- epoxy-17- methyl-(5α,6α)-morphinan-3,6-diol sulfate (2:1) (salt), pentahydrate, with the following structural formula:

(C17H19NO3)2 • H2SO4 • 5H2O Molecular Weight is 758.83

Morphine sulfate USP is an odorless, white crystalline powder with a bitter taste. It has a solubility of 1 in 21 parts of water and 1 in 1000 parts of alcohol, but is practically insoluble in chloroform or ether. The octanol:water partition coefficient of morphine is 1.42 at physiologic pH and the pKa is 7.9 for the tertiary nitrogen (the majority is ionized at pH 7.4).

Each mL of INFUMORPH 200 contains morphine sulfate, USP 10 mg (200 mg/20 mL) and sodium chloride 8 mg in Water for Injection, USP. Each mL of INFUMORPH 500 contains morphine sulfate, USP 25 mg (500 mg/20 mL) and sodium chloride 6.25 mg in Water for Injection, USP. If needed, sodium hydroxide and/or sulfuric acid are added for pH adjustment to 4.5. Contains no preservative. Each 20 mL ampul of INFUMORPH is intended for SINGLE USE ONLY.

12 CLINICAL PHARMACOLOGY

12.1 Mechanism of Action

Morphine is a full opioid agonist and is relatively selective for the mu-opioid receptor, although it can bind to other opioid receptors at higher doses. The principal therapeutic action of morphine is analgesia. Like all full opioid agonists, there is no ceiling effect for analgesia with morphine. Clinically, dosage is titrated to provide adequate analgesia and may be limited by adverse reactions, including respiratory and CNS depression.

The precise mechanism of the analgesic action is unknown. However, specific CNS opioid receptors for endogenous compounds with opioid-like activity have been identified throughout the brain and spinal cord and are thought to play a role in the analgesic effects of this drug.

12.2 Pharmacodynamics

Effects on the Central Nervous System

Morphine produces respiratory depression by direct action on brain stem respiratory centers. The respiratory depression involves a reduction in the responsiveness of the brain stem respiratory centers to both increases in carbon dioxide tension and electrical stimulation.

Morphine causes miosis, even in total darkness. Pinpoint pupils are a sign of opioid overdose but are not pathognomic (e.g., pontine lesions of hemorrhagic or ischemic origins may produce similar findings). Marked mydriasis rather than miosis may be seen due to hypoxia in overdose situations.

Both early and late respiratory depression (up to 24 hours post dosing) have been reported following neuraxial administration. Circulation of the spinal fluid may also result in high concentrations of morphine reaching the brain stem directly.

Effects on the Gastrointestinal Tract and Other Smooth Muscle

Morphine causes a reduction in motility associated with an increase in smooth muscle tone in the antrum of the stomach and duodenum. Digestion of food in the small intestine is delayed and propulsive contractions are decreased. Propulsive peristaltic waves in the colon are decreased, while tone may be increased to the point of spasm, resulting in constipation. Other opioid-induced effects may include a reduction in biliary and pancreatic secretions, spasm of sphincter of Oddi, and transient elevations in serum amylase, and opioid-induced esophageal dysfunction (OIED).

Effects on the Cardiovascular System

Morphine produces peripheral vasodilation which may result in orthostatic hypotension or syncope. Manifestations of histamine release and/or peripheral vasodilation may include pruritis, flushing, red eyes and sweating and/or orthostatic hypotension.

Effects on the Endocrine System

Opioids inhibit the secretion of adrenocorticotropic hormone (ACTH), cortisol, and lutenizing hormone (LH) in humans [see Adverse Reactions (6)]. They also stimulate prolactin, growth hormone (GH) secretion, and pancreatic secretion of insulin and glucagon.

Use of opioids for an extended period of time may influence the hypothalamic-pituitary-gonadal axis, leading to androgen deficiency that may manifest as low libido, impotence, erectile dysfunction, amenorrhea, or infertility. The causal role of opioids in the clinical syndrome of hypogonadism is unknown because the various medical, physical, lifestyle, and psychological stressors that may influence gonadal hormone levels have not been adequately controlled for in studies conducted to date [see Adverse Reactions (6)].

Effects on the Immune System

Opioids have been shown to have a variety of effects on components of the immune system in in vitro and animal models. The clinical significance of these findings is unknown. Overall, the effects of opioids appear to be modestly immunosuppressive.

Concentration – Efficacy Relationships

The minimum effective analgesic concentration will vary widely among patients, especially among patients who have been previously treated with opioid agonists. The minimum effective analgesic concentration of morphine for any individual patient may increase over time due to an increase in pain, the development of a new pain syndrome and/or the development of analgesic tolerance [see Dosage and Administration (2.1, 2.5)].

Concentration – Adverse Reaction Relationships

There is a relationship between increasing morphine plasma concentration and increasing frequency of dose-related opioid adverse reactions such as nausea, vomiting, CNS effects, and respiratory depression. In opioid-tolerant patients, the situation may be altered by the development of tolerance to opioid-related adverse reactions [see Dosage and Administration (2.1, 2.2, 2.6)].

12.3 Pharmacokinetics

Epidural Administration

Absorption

Morphine, injected into the epidural space, is rapidly absorbed into the general circulation. Absorption is so rapid that the plasma concentration-time profiles closely resemble those obtained after intravenous or intramuscular administration. Peak plasma concentrations averaging 33–40 ng/mL (range 5–62 ng/mL) are achieved within 10 to 15 minutes after administration of 3 mg of morphine.

Distribution

Plasma concentrations decline in a multiexponential fashion. CSF concentrations of morphine, after epidural doses of 2 to 6 mg in postoperative patients, have been reported to be 50 to 250 times higher than corresponding plasma concentrations. The CSF levels of morphine exceed those in plasma after only 15 minutes and are detectable for as long as 20 hours after the injection of 2 mg of epidural morphine. Approximately 4% of the dose injected epidurally reaches the CSF. This corresponds to the relative minimum effective epidural and intrathecal doses of 5 mg and 0.25 mg, respectively. The disposition of morphine in the CSF follows a biphasic pattern, with an early half-life of 1.5h and a late phase half-life of about 6 h. Morphine crosses the dura slowly, with an absorption half-life across the dura averaging 22 minutes. Maximum CSF concentrations are seen 60–90 minutes after injection. Minimum effective CSF concentrations for postoperative analgesia average 150 ng/mL (range < 1-380 ng/mL).

Elimination

The terminal half-life is reported to range from 39 to 249 minutes (mean of 90 ± 34.3 min) for epidural administration.

Metabolism

The major pathway of clearance is hepatic glucuronidation to morphine-3-glucuronide, which is pharmacologically inactive.

Excretion

The major excretion path of the morphine-3-glucuronide conjugate is through the kidneys, with about 10% in the feces. Morphine is also eliminated by the kidneys, 2 to 12% being excreted unchanged in the urine.

Intrathecal Administration

Absorption

Time-to-peak plasma concentrations, however, are similar (5-10 min) after either epidural or intrathecal bolus administration of morphine. Maximum plasma morphine concentrations after 0.3 mg intrathecal morphine have been reported from < 1 to 7.8 ng/mL. The minimum analgesic morphine plasma concentration during Patient Controlled Analgesia (PCA) has been reported as 20–40 ng/mL, suggesting that any analgesic contribution from systemic redistribution would be minimal after the first 30–60 minutes with epidural administration and virtually absent with intrathecal administration of morphine.

Distribution

The intrathecal route of administration circumvents meningeal diffusion barriers and, therefore, lower doses of morphine produce comparable analgesia to that induced by the epidural route. After intrathecal bolus injection of morphine, there is a rapid initial distribution phase lasting 15–30 minutes and a half-life in the CSF of 42–136 min (mean 90 ± 16 min). Derived from limited data, it appears that the disposition of morphine in the CSF, from 15 minutes postintrathecal administration to the end of a six-hour observation period, represents a combination of the distribution and elimination phases. Morphine concentrations in the CSF averaged 332 ± 137 ng/mL at 6 hours, following a bolus dose of 0.3 mg of morphine. The apparent volume of distribution of morphine in the intrathecal space is about 22 ± 8 mL.

13 NONCLINICAL TOXICOLOGY

13.1 Carcinogenesis, Mutagenesis, Impairment of Fertility

Carcinogenesis
Long-term studies in animals to evaluate the carcinogenic potential of morphine have not been conducted.
Mutagenesis
No formal studies to assess the mutagenic potential of morphine have been conducted. In the published literature, morphine was found to be mutagenic in vitro increasing DNA fragmentation in human T-cells. Morphine was reported to be mutagenic in the in vivo mouse micronucleus assay and positive for the induction of chromosomal aberrations in mouse spermatids and murine lymphocytes. Mechanistic studies suggest that the in vivo clastogenic effects reported with morphine in mice maybe related to increases in glucocorticoid levels produced by morphine in this species. In contrast to the above positive findings, in vitro studies in the literature have also shown that morphine did not induce chromosomal aberrations in human leukocytes or translocations or lethal mutations in Drosophila.
Impairment of Fertility
No formal nonclinical studies to assess the potential of morphine to impair fertility have been conducted.
Several nonclinical studies from the literature have demonstrated adverse effects on male fertility in the rat from exposure to morphine. One study in which male rats were administered morphine sulfate subcutaneously prior to mating (up to 30 mg/kg twice daily) and during mating (20 mg/kg twice daily) with untreated females, a number of adverse reproductive effects including reduction in total pregnancies and higher incidence of pseudopregnancies at 20 mg/kg/day (3.2 times the HDD) were reported.
Studies from the literature have also reported changes in hormonal levels in male rats (i.e., testosterone, luteinizing hormone) following treatment with morphine at 10 mg/kg/day or greater (1.6 times the HDD).
Female rats that were administered morphine sulfate intraperitoneally prior to mating exhibited prolonged estrous cycles at 10 mg/kg/day (1.6 times the HDD).

16 HOW SUPPLIED/STORAGE AND HANDLING

INFUMORPH (preservative-free morphine sulfate sterile solution), is, a preservative-free solution, supplied in amber ampuls for epidural or intrathecal administration via a continuous microinfusion device as follows:

NDC 0641-6039-01 INFUMORPH 200 200 mg/20 mL (10 mg/mL) Single Use amber ampuls packaged individually

NDC 0641-6040-01 INFUMORPH 500 500 mg/20 mL (25 mg/mL) Single Use amber ampuls packaged individually

INFUMORPH is supplied in sealed ampuls. Accidental dermal exposure should be treated by the removal of any contaminated clothing and rinsing the affected area with water.

PROTECT FROM LIGHT. Keep stored in carton until time of use. Store at 20˚‑25˚C (68˚‑77˚F), excursions permitted to 15˚‑30˚C (59˚‑86˚F) [See USP Controlled Room Temperature]. DO NOT FREEZE. INFUMORPH contains no preservative or antioxidant. Each 20 mL ampul of INFUMORPH is intended for SINGLE USE ONLY. Discard any unused portion. Do not heat-sterilize.

To report SUSPECTED ADVERSE REACTIONS, contact Hikma Pharmaceuticals USA Inc. at 1-877-845-0689, or the FDA at 1-800-FDA-1088 or www.fda.gov/medwatch. For Product Inquiry call 1-877-845-0689.

17 PATIENT COUNSELING INFORMATION

Addiction, Abuse, and Misuse

Inform patients that the use of INFUMORPH, even when taken as recommended, can result in addiction, abuse, and misuse, which can lead to overdose and death [see Warnings and Precautions (5.2)].

Life-Threatening Respiratory Depression

Inform patients of the risk of life-threatening respiratory depression, including information that the risk is greatest when starting INFUMORPH or when the dosage is increased, and that it can occur even at recommended dosages [see Warnings and Precautions (5.3)]. Advise patients how to recognize respiratory depression and to seek medical attention if breathing difficulties develop.

Hyperalgesia and Allodynia

Advise patients to inform their healthcare provider if they experience symptoms of hyperalgesia, including worsening pain, increased sensitivity to pain, or new pain [see Warnings and Precautions (5.8); Adverse Reactions (6.2)].

Serotonin Syndrome

Inform patients that INFUMORPH could cause a rare but potentially life-threatening condition resulting from concomitant administration of serotonergic drugs. Warn patients of the symptoms of serotonin syndrome and to seek medical attention right away if symptoms develop after discharge from the hospital. Instruct patients to inform their physicians if they are taking, or plan to take serotonergic medications [see Drug Interactions (7)].

MAOI Interaction

Inform patients not to take INFUMORPH while using any drugs that inhibit monoamine oxidase. Patients should not start MAOIs while taking INFUMORPH [see Warnings and Precautions (5.10), Drug Interactions (7)].

Driving or Operating Heavy Machinery

Inform patients that INFUMORPH may impair the ability to perform potentially hazardous activities such as driving a car or operating heavy machinery. Advise patients not to perform such tasks until they know how they will react to the medication [see Warnings and Precautions (5.17)].

Constipation

Advise patients of the potential for severe constipation, including management instructions and when to seek medical attention [see Adverse Reactions (6)].

Hypotension

Inform patients that INFUMORPH may cause orthostatic hypotension and syncope. Instruct patients how to recognize symptoms of low blood pressure and how to reduce the risk of serious consequences should hypotension occur (e.g., sit or lie down, carefully rise from a sitting or lying position) [see Warnings and Precautions (5.12)].

Anaphylaxis

Inform patients that anaphylaxis have been reported with ingredients contained in INFUMORPH. Advise patients how to recognize such a reaction and when to seek medical attention [see Contraindications (4), Adverse Reactions (6)].

Pregnancy

Neonatal Opioid Withdrawal Syndrome

Inform female patients of reproductive potential that use of INFUMORPH for an extended period of time during pregnancy can result in neonatal opioid withdrawal syndrome, which may be life-threatening if not recognized and treated [see Warnings and Precautions (5.5), Use in Specific Populations (8.1)].

Embryo-Fetal Toxicity

Inform female patients of reproductive potential that INFUMORPH can cause fetal harm and to inform the healthcare provider of a known or suspected pregnancy [see Use in Specific Populations (8.3)].

Lactation

Advise nursing mothers to monitor infants for increased sleepiness (more than usual), breathing difficulties, or limpness. Instruct nursing mothers to seek immediate medical care if they notice these signs [see Use in Specific Populations (8.2)].

Infertility

Inform patients that use of opioids for an extended period of time may cause reduced fertility. It is not known whether these effects on fertility are reversible [see Adverse Reactions (6)].

Manufactured by:
Hikma Pharmaceuticals USA Inc.
Berkeley Heights, NJ 07922

462-217-06

PRINCIPAL DISPLAY PANEL

NOT for IV, IM or Subcutaneous Injection
NDC 0641-6039-01 20 mL Single Dose Ampul
INFUMORPH 200 Rx only
(Preservative-free Morphine Sulfate Sterile Solution) CII
200 mg per 20 mL (10 mg/mL)
For Neuraxial Administration in
Continuous Microinfusion Devices

NOT for Intravenous, Intramuscular or Subcutaneous Injection
NDC 0641-6039-01 20 mL Single Dose Ampul
Infumorph 200 Rx only
(Preservative-free Morphine Sulfate Sterile Solution) CII
200 mg per 20 mL
(10 mg/mL)
For Neuraxial
Administration
in Continuous
Microinfusion Devices

PRINCIPAL DISPLAY PANEL

NOT for IV, IM or Subcutaneous Injection
NDC 0641-6040-01 20 mL Single Dose Ampul
INFUMORPH 500 Rx only
(Preservative-free Morphine Sulfate Sterile Solution) CII
500 mg per 20 mL (25 mg/mL)
For Neuraxial Administration in
Continuous Microinfusion Devices

NOT FOR IV, IM, or SC INJECTION
NDC 0641-6040-01 20 mL Single Dose Ampul
INFUMORPH 500
(Preservative-free Morphine Sulfate Sterile Solution) CII
500 mg per 20 mL

(25 mg/mL)

FOR NEURAXIAL ADMINISTRATION
IN CONTINUOUS MICROINFUSION DEVICES